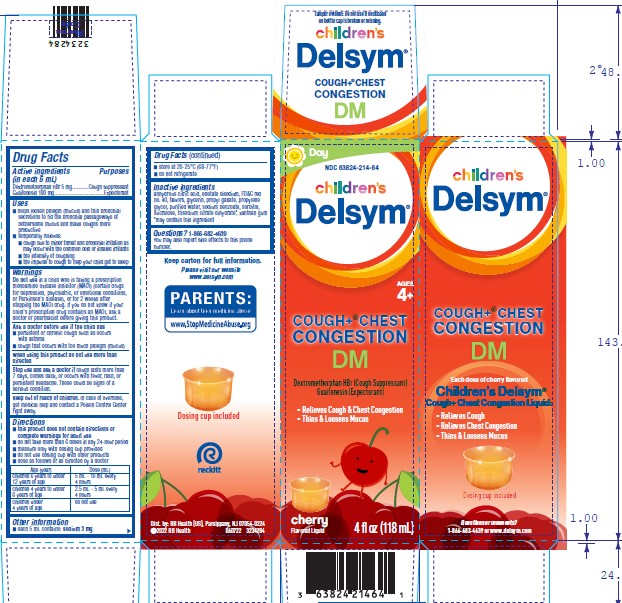 DRUG LABEL: Childrens Delsym
NDC: 63824-214 | Form: SOLUTION
Manufacturer: RB Health (US) LLC
Category: otc | Type: HUMAN OTC DRUG LABEL
Date: 20240628

ACTIVE INGREDIENTS: DEXTROMETHORPHAN HYDROBROMIDE 5 mg/5 mL; GUAIFENESIN 100 mg/5 mL
INACTIVE INGREDIENTS: ANHYDROUS CITRIC ACID; EDETATE DISODIUM; FD&C RED NO. 40; GLYCERIN; PROPYLENE GLYCOL; PROPYL GALLATE; WATER; SODIUM BENZOATE; SORBITOL; SUCRALOSE; TRISODIUM CITRATE DIHYDRATE; XANTHAN GUM

Children's Delsym®
Cough Plus® Chest Congestion DM

Drug Facts

ACTIVE INGREDIENT

PURPOSE

Active ingredients (in each 5 mL) | Purposes
Dextromethorphan HBr 5 mg | Cough suppressant
Guaifenesin 100 mg | Expectorant

Uses

- helps loosen phlegm (mucus) and thin bronchial secretions to rid the bronchial passageways of bothersome mucus and make coughs more productive
- temporarily relieves:
  - cough due to minor throat and bronchial irritation as may occur with the common cold or inhaled irritants
  - the intensity of coughing
  - the impulse to cough to help your child get to sleep

Warnings

Do not use in a child who is taking a prescription monoamine oxidase inhibitor (MAOI) (certain drugs for depression, psychiatric, or emotional conditions, or Parkinson's disease), or for 2 weeks after stopping the MAOI drug. If you do not know if your child's prescription drug contains an MAOI, ask a doctor or pharmacist before giving this product.

Ask a doctor before use if the child has

- persistent or chronic cough such as occurs with asthma
- cough that occurs with too much phlegm (mucus)

When using this product do not use more than directed

Stop use and ask a doctor if

- cough lasts more than 7 days, comes back, or occurs with fever, rash, or headache that lasts. These could be signs of a serious condition.

Keep out of reach of children. In case of overdose, get medical help or contact a Poison Control Center right away.

Directions

- this product does not contain directions or complete warnings for adult use
- do not give more than 6 doses in any 24-hour period
- measure only with dosing cup provided
- do not use dosing cup with other products
- dose as follows or as directed by a doctor

Age (year) | Dose (mL)
children 6 to under 12 years of age | 5 mL - 10 mL every 4 hours
children 4 to under 6 years of age | 2.5 mL - 5 mL every 4 hours
children under 4 years of age | do not use

Other information

- each 5 mL contains: sodium 3 mg
- store at 20-25°C (68-77°F)
- do not refrigerate

Inactive ingredients

anhydrous citric acid, edetate disodium, FD&C red no. 40, flavors, glycerin, propyl gallate, propylene glycol, purified water, sodium benzoate, sorbitol, sucralose, trisodium citrate dihydrate [may contain this ingredient] , xanthan gum

Questions?

1-866-682-4639

You may also report side effects to this phone number.

Dist. by: RB Health (US), Parsippany, NJ 07054-0224

PRINCIPAL DISPLAY PANEL - 118 mL Bottle Carton

NDC 63824-214-64
Ages 4 Years +

Children's
Delsym®

COUGH +®
Chest Congestion

DM

Dextromethorphan HBr (Cough Suppressant)
Guaifenesin (Expectorant)

- Relieves Cough
- Relieves Chest
  Congestion
- Thins &
  Loosens
  Mucus

Cherry Flavor

4 fl oz (118 mL)